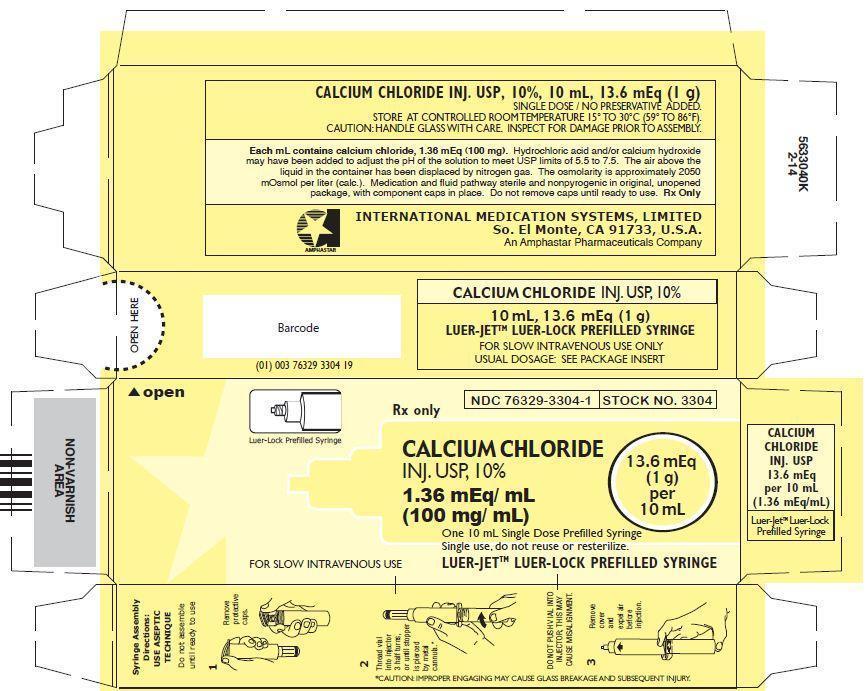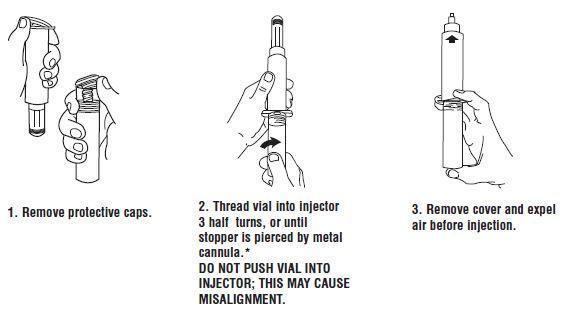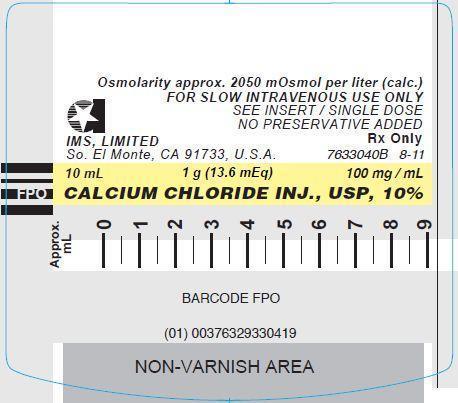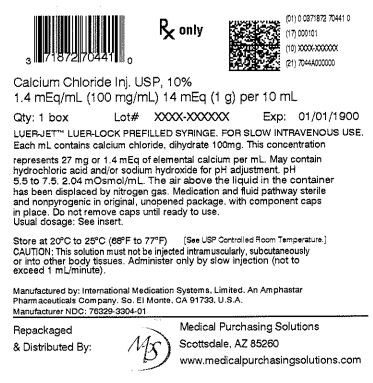 DRUG LABEL: Calcium Chloride
NDC: 71872-7044 | Form: INJECTION
Manufacturer: Medical Purchasing Solutions, LLC
Category: prescription | Type: HUMAN PRESCRIPTION DRUG LABEL
Date: 20230530

ACTIVE INGREDIENTS: CALCIUM CHLORIDE 100 mg/1 mL
INACTIVE INGREDIENTS: HYDROCHLORIC ACID; CALCIUM HYDROXIDE

CALCIUM CHLORIDE
INJECTION, USP, 10%

13.6 mEq (1 g) per 10 mL
100 mg (1.36 mEq)/ mL
Osmolarity approximately 2050 mOsmol/L

DESCRIPTION

Calcium Chloride Injection, USP, 10%, is a sterile aqueous solution containing, in each mL, 100 mg (1.36 mEq) calcium chloride. The pH of the solution may have been adjusted with hydrochloric acid and / or calcium hydroxide, when necessary. The air above the liquid in the individual containers has been displaced by flushing with nitrogen during the filling operation. The preparation contains no antimicrobial preservatives and is intended as a single-dose vial; once the unit is assembled and used, any remaining portion of the solution must be discarded with the entire unit.

Calcium Chloride, USP, contains two molecules of water of hydration and is chemically designated as CaCl2 • 2H20.

CLINICAL PHARMACOLOGY

Calcium is the fifth most abundant element in the body, the major fraction of which is found in the bony structure. Calcium plays important physiological roles; it is essential for the functional integrity of the nervous and muscular systems; it is necessary for normal cardiac function; and it is one of the factors involved in the mechanism of blood coagulation.

INDICATIONS AND USAGE

Calcium Chloride Injection, USP, 10% is indicated:

In the treatment of hypocalcemia in conditions requiring a prompt increase in plasma calcium levels (e.g., neonatal tetany and tetany due to parathyroid deficiency, vitamin D deficiency and alkalosis) and for prevention of hypocalcemia during exchange transfusions.

As adjunctive therapy in the management of acute symptoms in lead colic.

In the treatment of magnesium intoxication due to overdosage of magnesium sulfate.

In severe hyperkalemia, to combat deleterious effects on electrocardiographic (ECG) function, pending correction of the potassium level in the extracellular fluid.

In cardiac resuscitation, particularly after open heart surgery, when epinephrine fails to improve weak or ineffective myocardial contractions.

CONTRAINDICATIONS

Calcium chloride is contraindicated for cardiac resuscitation in the presence of ventricular fibrillation.

WARNINGS

Calcium chloride should be injected into a large vein very slowly, as it may cause peripheral vasodilatation and a cutaneous burning sensation. A moderate fall in blood pressure due to vasodilatation may attend the injection. Since calcium chloride is an acidifying salt, it is usually undesirable in the treatment of hypocalcemia or renal insufficiency.

PRECAUTIONS

General

Calcium Chloride Injection, USP, 10% is irritating to veins and must not be injected into tissues, since severe necrosis and sloughing may occur. Great care should be taken to avoid extravasation or accidental injection into perivascular tissues.

Solutions should be warmed to body temperature. Injections should be made slowly through a small needle into a large vein to minimize venous irritation and avoid undesirable reactions. It is particularly important to prevent a high concentration of calcium from reaching the heart because of the danger of cardiac syncope. If injected into the ventricular cavity in cardiac resuscitation care must be taken to avoid injection into the myocardial tissue.

Drug Interactions

Because of the danger involved in the simultaneous use of calcium salts and drugs of the digitalis group, a digitalized patient should not receive an intravenous injection of a calcium compound unless the indications are clearly defined.

Calcium salts should not generally be mixed with carbonates, phosphates, sulfates or tartrates in parenteral admixtures.

ADVERSE REACTIONS

Rapid I.V. injection may cause the patient to complain of tingling sensations, a calcium taste, a sense of oppression or “heat wave.”

Injections of calcium chloride are accompanied by peripheral vasodilation as well as a local “burning” sensation, and there may be a moderate fall in blood pressure.

DOSAGE AND ADMINISTRATION FOR INTRACARDIAC OR INTRAVENOUS USE ONLY

INJECT SLOWLY
Calcium Chloride Injection, USP, 10%, is administered only by slow intravenous injection (not to exceed 1 mL/min) and / or in cardiac resuscitation, by injection into the ventricular cavity. It must not be injected into the myocardium.

The usual precautions for intravenous therapy should be observed. If time permits, the solution should be warmed to body temperature. The injection should be halted if the patient complains of any discomfort; it may be resumed when symptoms disappear. Following injection, the patient should remain recumbent for a short time.

INTRACARDIAC USE
For cardiac resuscitation, inject into the ventricular cavity, not into the heart muscle.

Usual Adult Dosage: 200 to 800 mg (2 to 8 mL) when injected into the ventricular cavity.

Pediatric Dosage: 0.2 mL/kg of body weight.

INTRAVENOUS USE
Hypocalcemic Disorders

Usual Adult Dosage: 500 mg to 1 g (5 to 10 mL) at intervals of 1 to 3 days, depending on the response of the patient and / or results of serum calcium determinations. Repeated injections may be required because of rapid excretion of calcium.

Pediatric Dosage: 0.2 mL /kg of body weight. Maximum 1-10 mL/day.

Magnesium Intoxication
Initial Adult Dose: 500 mg (5 mL) administered promptly and the patient observed for signs of recovery before further doses are given.

Hyperkalemic ECG Disturbances of Cardiac Function
Dosage should be adjusted by constant monitoring of ECG changes during administration.

HOW SUPPLIED

CALCIUM CHLORIDE INJECTION, USP, 10%

In unit-use packages containing a Luer-Jet™ Luer-Lock Prefilled Syringe.

Stock No. 3304 NDC 76329-3304-1 10 mL

Ten cartons per package.

Syringe Assembly Directions:
USE ASEPTIC TECHNIQUE
Do not assemble until ready to use.

*CAUTION: IMPROPER ENGAGING MAY CAUSE GLASS BREAKAGE AND SUBSEQUENT INJURY.

Store at controlled room temperature 15° to 30°C (59° to 86°F).

Rx Only

INTERNATIONAL MEDICATION SYSTEMS, LIMITEDSo. El Monte, CA 91733, U.S.A. Rev. 2-13
An Amphastar Pharmaceuticals Company

© INTERNATIONAL MEDICATION SYSTEMS, LIMITED 2013

PRINCIPLE DISPLAY PANEL: Syringe Label

Osmolarity approx. 2050 mOsmol per liter (calc.)

FOR SLOW INTRAVENOUS USE ONLY

SEE INSERT / SINGLE DOSE

NO PRESERVATIVE ADDED

IMS, LIMITED

Rx Only

So. El Monte, CA 91733, U.S.A.

7633040B 8-11

10 mL 1 g (13.6 mEq) 100 mg / mL

CALCIUM CHLORIDE INJ., USP, 10%

Approx. mL 0 1 2 3 4 5 6 7 8 9

PRINCIPLE DISPLAY PANEL: Carton

Luer-Lock Prefilled Syringe

Rx only

NDC 76329-3304-1

STOCK NO. 3304

CALCIUM CHLORIDE INJ. USP, 10%

1.36 mEq/ mL (100 mg/ mL)

13.6 mEq (1 g) per 10 mL

One 10 mL Single Dose Prefilled Syringe

Single use, do not reuse or resterilize.

FOR SLOW INTRAVENOUS USE

LUER-JETTM LUER-LOCK PREFILLED SYRINGE

PRINCIPAL DISPLAY PANEL: Outer package label

NDC 71872-7044-1

1 - Prefilled Syringe

Calcium Chloride Inj. USP, 10%

Rx Only